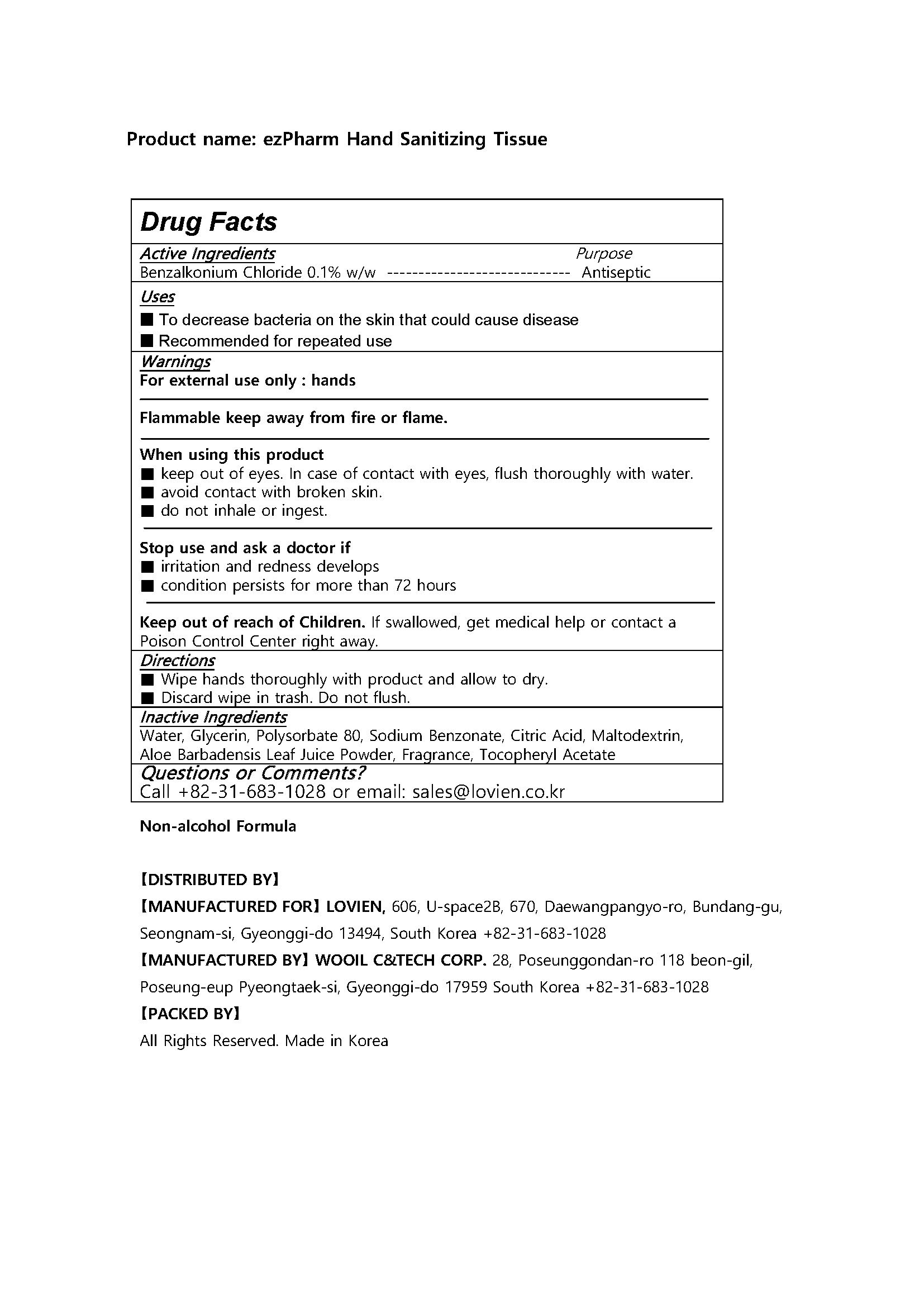 DRUG LABEL: ezPharm Hand Sanitizing Tissue
NDC: 58474-001 | Form: LIQUID
Manufacturer: WOOIL C&TECH.CORP
Category: otc | Type: HUMAN OTC DRUG LABEL
Date: 20200704

ACTIVE INGREDIENTS: BENZALKONIUM CHLORIDE 0.1 g/100 mL
INACTIVE INGREDIENTS: .ALPHA.-TOCOPHEROL ACETATE; WATER; GLYCERIN; SODIUM BENZOATE; MALTODEXTRIN; ALOE VERA LEAF; POLYSORBATE 80

Drug Facts

ACTIVE INGREDIENT

benzalkonium

INACTIVE INGREDIENT

Water, Glycerin, Polysorbate 80, Sodium Benzonate, Citric Acid, Maltodextrin, Aloe Barbadensis Leaf Juice Powder, Fragrance, Tocopheryl Acetate

PURPOSE

■ To decrease bacteria on the skin that could cause disease

■ Recommended for repeated use

KEEP OUT OF REACH OF THE CHILDREN

INDICATIONS AND USAGE

■ Wipe hands thoroughly with product and allow to dry.

■ Discard wipe in trash. Do not flush.

WARNINGS

■ keep out of eyes. In case of contact with eyes, flush thoroughly with water.

■ avoid contact with broken skin.

■ do not inhale or ingest.

DOSAGE AND ADMINISTRATION

external use only